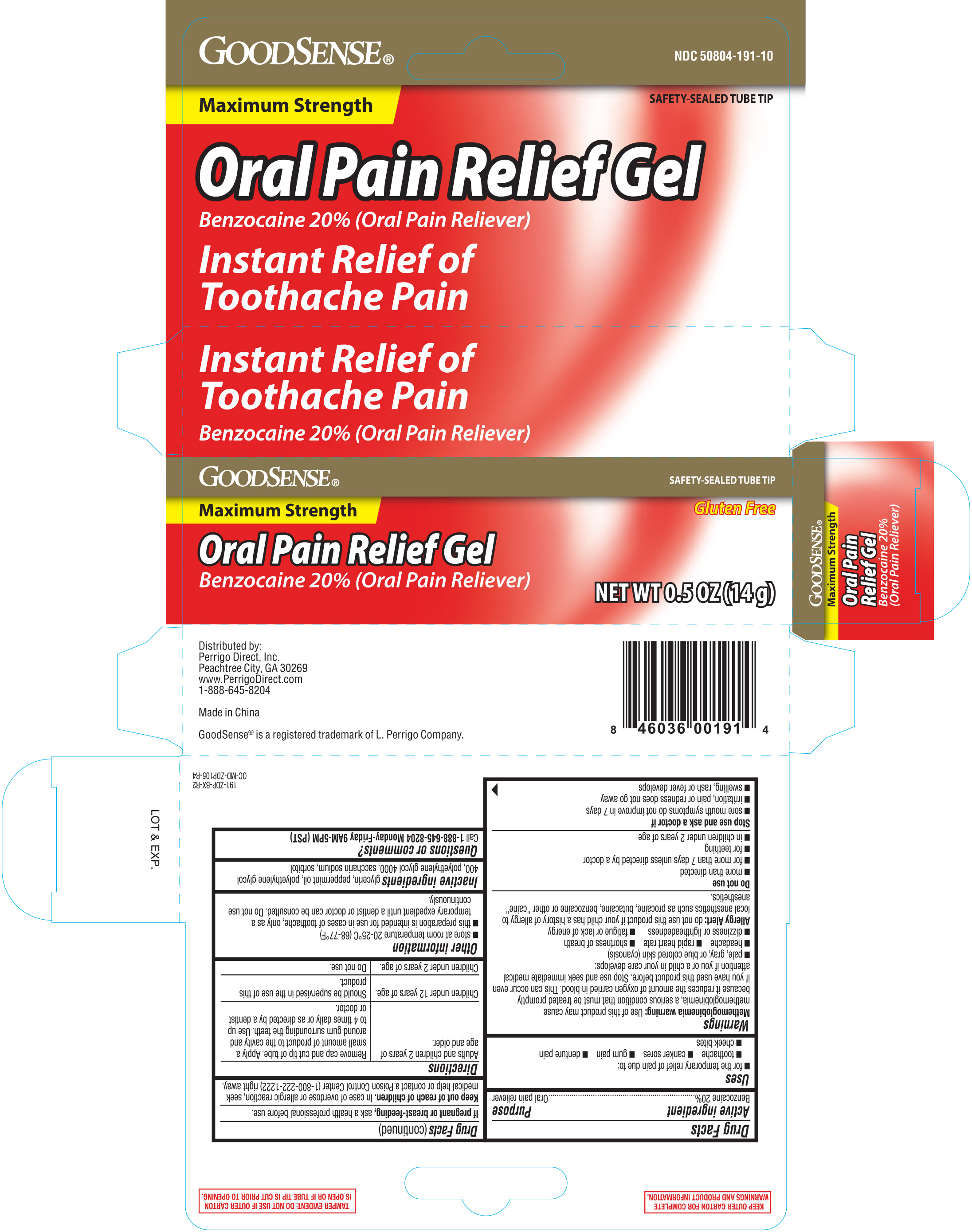 DRUG LABEL: Goodsense Oral Pain Relief
NDC: 50804-191 | Form: GEL
Manufacturer: Geiss, Destin and Dunn, Inc.
Category: otc | Type: HUMAN OTC DRUG LABEL
Date: 20260112

ACTIVE INGREDIENTS: BENZOCAINE 20 g/100 g
INACTIVE INGREDIENTS: POLYETHYLENE GLYCOL 400; POLYETHYLENE GLYCOL 4000; SACCHARIN SODIUM; SORBITOL; MINT; GLYCERIN

GoodSense Oral Pain Relief Gel 0.5oz (191)

Active ingredient Purpose

Benzocaine 20%................................................. Oral pain reliever

Uses

- for the temporary relief of pain due to:
- toothache
- canker sores
- gum pain
- denture pain
- cheek bites

Warnings

Methemoglobinemia warning: Use of this product may cause methemoglobinemia, a serious condition that must be treated promptly because it reduces the amount of oxygen carried in blood. This can occur even if you have use this product before. Stop use and seek immediate medical attention if you or a child in your care develops:

- pale, gray, or blue colored skin (cyanosis)
- headache
- rapid heart rate
- shortness of breath
- dizziness or lightheadedness
- fatigue or lack of energy

Allergy Alert: do not use this product if your child has a history of allergy to local anesthetics such as procaine, butacaine, benzocaine or other "caine" anesthetics.

Do not use

- more than directed
- for more than 7 days unless directed by a doctor
- for teething
- in children under 2 years of age

Stop use and ask a doctor if

- sore mouth symptoms do not improve in 7 days
- irritation, pain, or redness does not go away
- swelling, rash or fever develops

PREGNANCY OR BREAST FEEDING

If pregnant or breast-feeding, ask a health professional before use.

Keep out of reach of children. If swallowed, get medical help or contact a Poison Control Center (1-800-222-1222) right away.

Directions

Adults and children 2 years of age and older | Remove cap and cut tip of tube. Apply a small amount of product to the cavity and around gum surrounding the teeth. Use up to 4 times daily or as directed by a dentist or doctor.
Children under 12 years of age. | Should be supervised in the use of this product.
Children under 2 years of age. | Do not use.

Other information

- store at 20-25°C (68°-77°F)
- this preparation is intended for use in cases of toothaches, only as a temporary expedient until a dentist or doctor can be consulted
- do not use continuously

INACTIVE INGREDIENT

Inactive ingredients: glycerin, peppermint oil, polyethylene glycol 400, polyethylene glycol 4000, saccharin sodium, sorbitol

Questions or comments?

Call 1-888-645-8204 Monday - Friday 9AM-5PM (PST)

DOSAGE AND ADMINISTRATION

Distributed by:

Perrigo Direct, Inc.

Peachtree City, GA 30269

www.PerrigoDirect.com

1-888-645-8204

Made in China